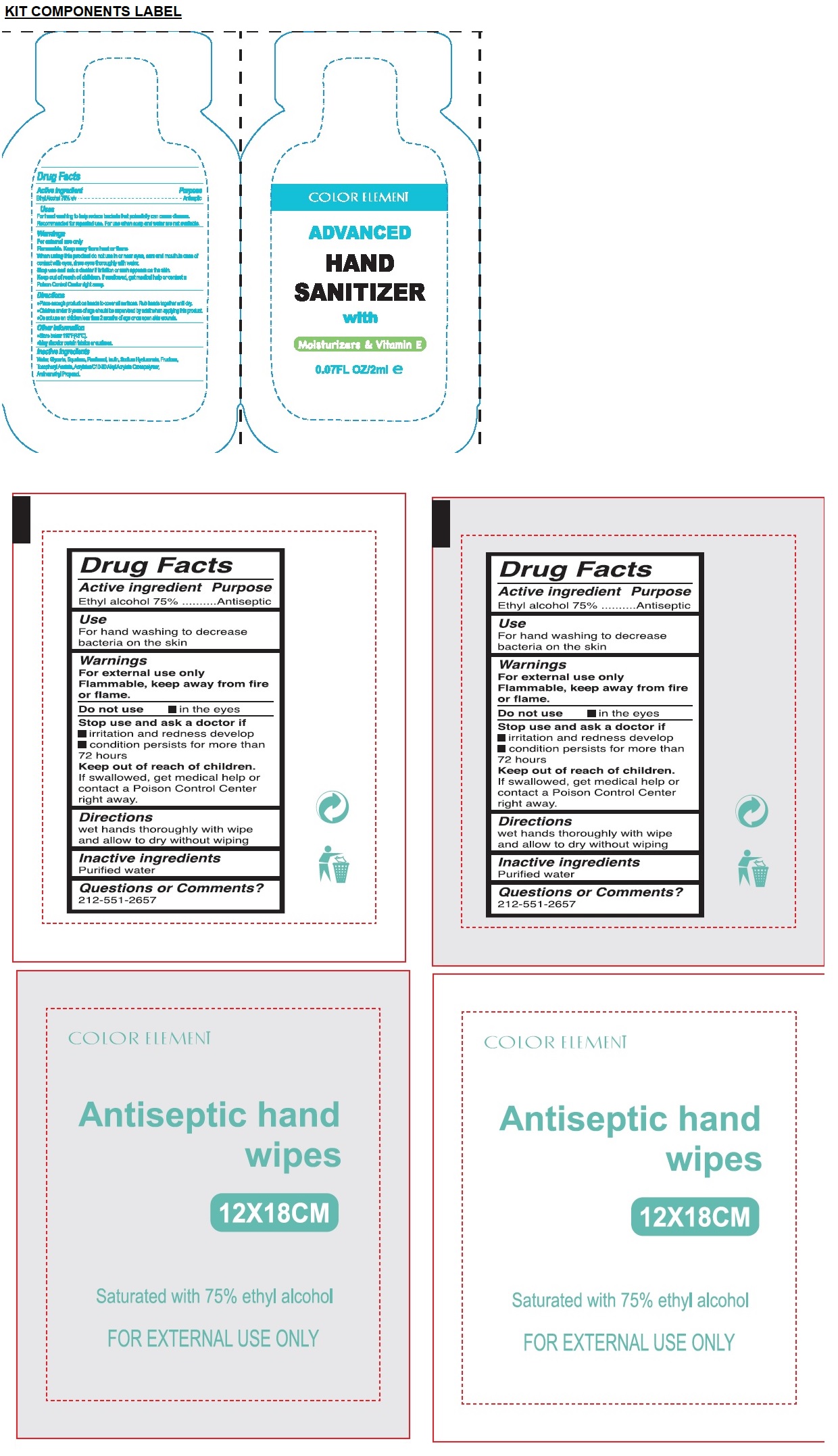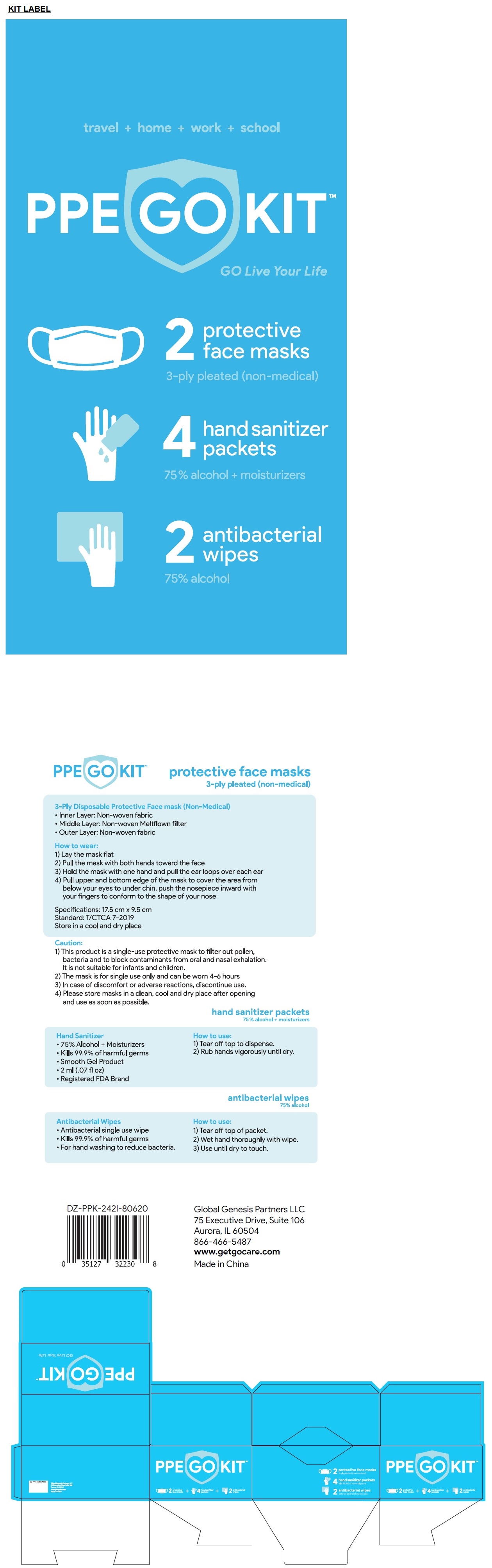 DRUG LABEL: PPE GO Kit
NDC: 79110-151 | Form: KIT | Route: TOPICAL
Manufacturer: Global Genesis Partners Llc
Category: otc | Type: HUMAN OTC DRUG LABEL
Date: 20200808

ACTIVE INGREDIENTS: ALCOHOL 0.75 mL/1 mL; ALCOHOL 0.75 mL/1 mL
INACTIVE INGREDIENTS: WATER; GLYCERIN; SQUALANE; PANTHENOL; INULIN; HYALURONATE SODIUM; FRUCTOSE; .ALPHA.-TOCOPHEROL ACETATE; AMINOMETHYLPROPANOL; WATER

PPE GO KIT

Color Element Hand Sanitizer with Moisturizers and Vitamin E

Drug Facts

Active ingredient

Ethyl Alcohol 75% v/v

Purpose

Antiseptic

Uses

- For hand washing to help reduce bacteria that potentially can cause disease. Recommended for repeated use. For use when soap and water are not available.

Warnings

For external use only.
Flammable. Keep away from fire and flame
When using this product do not use in or near the eyes, ears and mouth. In case of contact with eyes, rinse eyes thoroughly with water.
Stop use and ask a doctor if irritation or rash appears on the skin.

Keep out of reach of children. If swallowed, get medical help or contact a Poison Control Center right away.

Directions

- Place enough product on hands to cover all surfaces. Rub hands together until dry.
- Children under 6 years of age should be supervised by adult when applying this product.
- Do not use on children less than 2 months of age or on open skin wounds.

Other information

- Store between 15-30°C (59-86°F)
- May discolor some fabrics or surfaces

Inactive ingredients

Water, Glycerin, Squalane, Panthenol, Inulin, Sodium Hyaluronate, Fructose, Tocopheryl Acetate, Acrylates/C10-30 Alkyl Acrylate Crosspolymer, Aminomethyl Propanol.

Color Element Antiseptic Hand wipes saturated with 75% Ethyl Alcohol

Drug Facts

Active ingredient

Ethyl alcohol 75%

Purpose

Antiseptic

Use

For hand washing to decrease bacteria on the skin

Warnings

For external use only

Flammable, keep away from fire or flame.

Do not use • in the eyes

Stop use and ask a doctor if

• irritation and redness develop

• condition persists for more than 72 hours

Keep out of reach of children.

If swallowed, get medical help or contact a Poison Control Center right away.

Directions

wet hands thoroughly with wipe and allow to dry without wiping

Inactive ingredients

Purified water

Questions or Comments?

212-551-2657

PPE GO KIT™

Go Live Your Life

2 protective face masks 3-ply pleated (non-medical)

4 hand sanitizer packets 75% alcohol + moisturizers

2 antibacterial wipes 75% alcohol

3-Ply Disposable Protective Face mask (Non-Medical)

- Inner Layer: Non-woven fabric
- Middle Layer: Non-woven Meltflown filter
- Outer Layer: Non-woven fabric

How to wear:

1) Lay the mask flat

2) Pull the mask with both hands toward the face

3) Hold the mask with one hand and pull the ear loops each ear

4) Pull upper and bottom edge of the mask to cover the area from below your eyes to under chin, push the nosepiece inward with your fingers to conform to the shape of your nose

Specifications: 17.5 cm x 9.5 cm
Standard: T/CTCA 7-2019
Store in a cool and dry place

Caution:

1) This product is a single-use protective mask to filter out pollen, bacteria and to block contaminants from oral and nasal exhalation. It is not suitable for infants and children.

2) The mask is for single use only and can be worn 4-6 hours

3) In case of discomfort or adverse reactions, discontinue use.

4) Please store masks in a clean, cool and dry place after opening and use as soon as possible.

hand sanitizer packets 75% alcohol + moisturizers

Hand Sanitizer

- 75% Alcohol + Moisturizers
- Kills 99.9% of harmful germs
- Smooth Gel Product
- 2 ml (.07 fl oz)
- Registered FDA Brand

How to use:

1) Tear off top to dispense.
2) Rub hands vigorously until dry.

antibacterial wipes 75% alcohol

Antibacterial Wipes

- Antibacterial single use wipe
- Kills 99.9% of harmful germs
- For hand washing to reduce bacteria.

How to use:

1) Tear off top of packet.

2) Wet hand thoroughly with wipe.

3) Use until dry to touch.

Global Genesis Partners LLC

75 Executive Drive, Suite 106

Aurora, IL 60504

866-466-5487

www.getgocare.com

Made in China